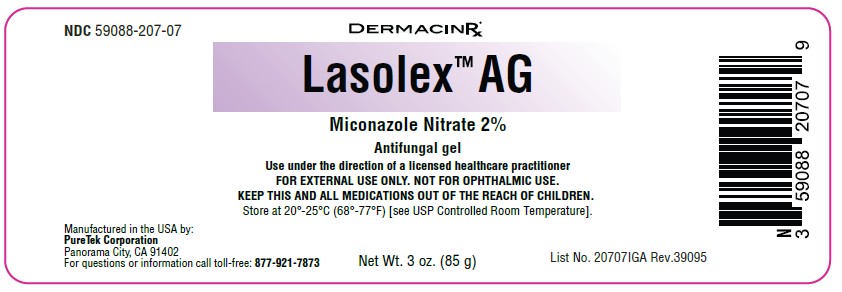 DRUG LABEL: Lasolex AG
NDC: 59088-207 | Form: GEL
Manufacturer: Puretek Corporation
Category: otc | Type: HUMAN OTC DRUG LABEL
Date: 20251231

ACTIVE INGREDIENTS: MICONAZOLE NITRATE 2 g/100 g
INACTIVE INGREDIENTS: GLYCERIN; SODIUM HYALURONATE; DIMETHICONE CROSSPOLYMER; ETHYLHEXYLGLYCERIN; HEXYLENE GLYCOL; PEG-4; DIMETHICONE; ALOE BARBADENSIS LEAF JUICE; PHENOXYETHANOL; PROPYLENE GLYCOL; DIMETHYL SULFOXIDE; AQUA; CAPRYLYL GLYCOL; HYDROXYETHYL CELLULOSE (5000 CPS AT 1%)

Lasolex AG
(Miconazole Nitrate 2%) Antifungal Gel

Active ingredient

Miconazole Nitrate 2%

Purpose

Anti-Fungal

Uses

- For the treatment of most athlete's foot (tinea pedis), jock itch (tinea cruris), and ringworm (tinea corporis)
- For relief of itching, scaling, cracking, burning, redness, soreness, irritation, discomfort

Warnings

For external use only. Not for opthalmic use.

Do not use

on children under 2 years of age unless directed by Doctor.

When using this product

Avoid contact with eyes.

Stop use and ask a doctor if

- irritation occurs or if there is no improvement within 4 weeks, discontinue use and consult a doctor (for athlete's foot and ringworm)
- irritation occurs or if there is no improvement within 2 weeks, discontinue use and consult a doctor (for jock itch)

Keep out of reach of children

If swallowed, get medical help or contact a Poison Control Center right away.

Directions

● Wash the affected area and dry thoroughly.

● Apply a thin layer of the product over affected area twice daily (morning and night) or

as directed by a doctor.

● Supervise children in the use of this product.

● For athlete's foot: Pay special attention to spaces between the toes; wear well-fitting, ventilated shoes, and change shoes and

socks at least once daily.

● For athlete's foot and ringworm, use daily for 4 weeks; for jock itch, use daily for 2 weeks.

● If condition persists longer, consult a doctor.

● This product is not effective on the scalp or nails.

Other Information

Store at 20° to 25°C (68° to 77°F) [see USP Controlled RoomTemperature]. Avoid excessive heat. Do not use if package is damaged.

Inactive Ingredients:

Aloe Barbadensis (Aloe Vera) Leaf Juice, Aqua (Purified Water), Caprylyl Glycol, Dimethicone, Dimethyl Sulfoxide, Dimethicone Crosspolymer, Ethylhexylglycerin, Glycerin, Hexylene Glycol, Hydroxyethylcellulose, PEG-4, Phenoxyethanol, Propylene Glycol, Sodium Hyaluronate.